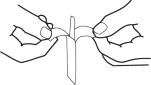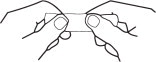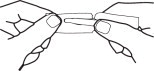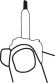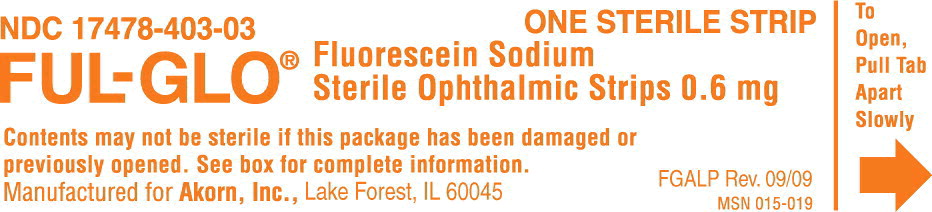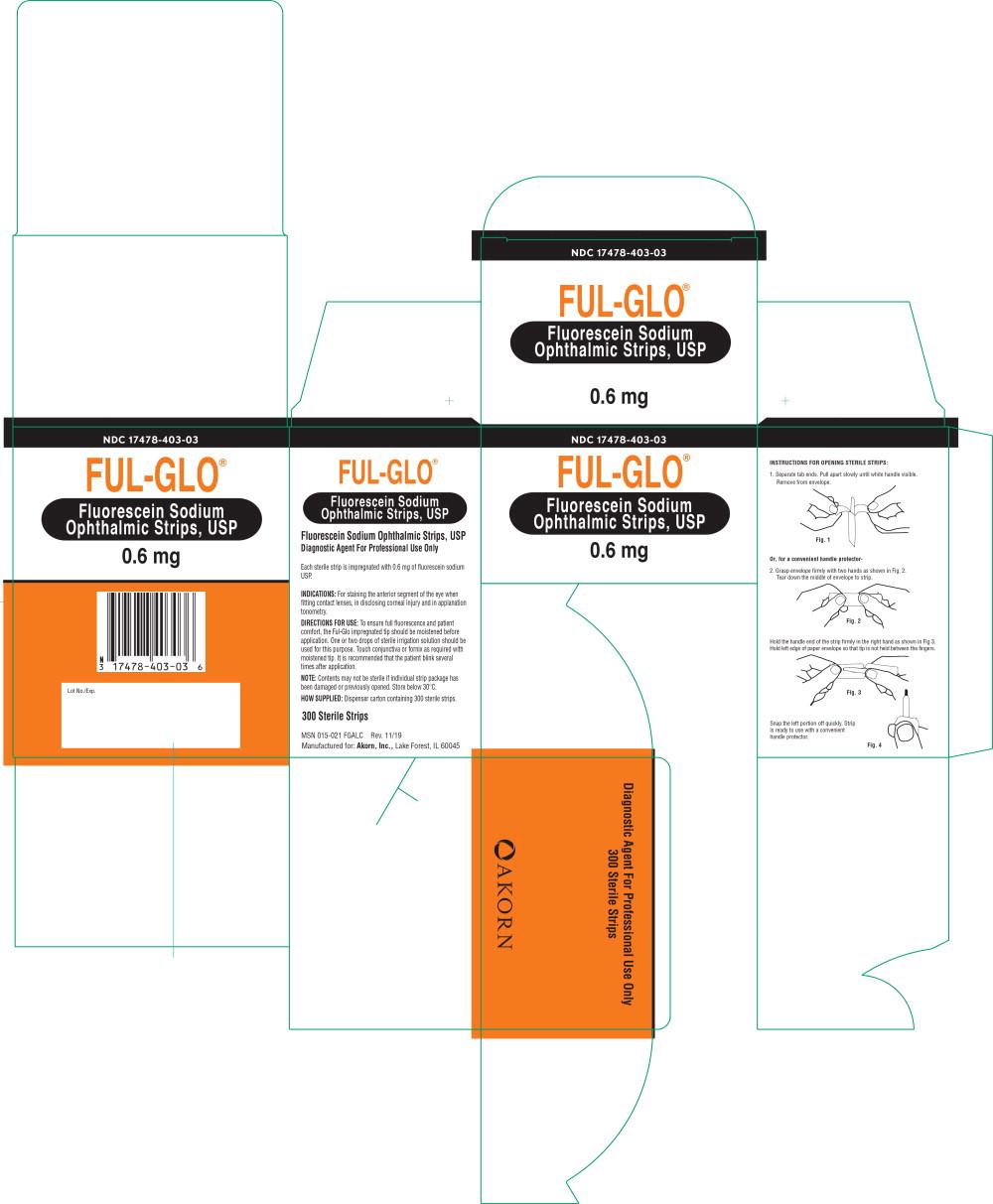 DRUG LABEL: FUL-GLO
NDC: 17478-403 | Form: STRIP
Manufacturer: Akorn
Category: prescription | Type: HUMAN PRESCRIPTION DRUG LABEL
Date: 20220912

ACTIVE INGREDIENTS: Fluorescein Sodium 0.6 mg/1 1

Fluorescein Sodium Ophthalmic Strips, USP

Diagnostic Agent For Professional Use Only

Each sterile strip is impregnated with 0.6 mg of fluorescein sodium USP.

INDICATIONS:

For staining the anterior segment of the eye when fitting contact lenses, in disclosing corneal injury and in applanation tonometry.

DIRECTIONS FOR USE:

To ensure full fluorescence and patient comfort, the Ful-Glo impregnated tip should be moistened before application. One or two drops of sterile irrigation solution should be used for this purpose. Touch conjunctiva or fornix as required with moistened tip. It is recommended that the patient blink several times after application.

NOTE: Contents may not be sterile if individual strip package has been damaged or previously opened. Store below 30°C.

INSTRUCTIONS FOR OPENING STERILE STRIPS:

1. Separate tab ends. Pull apart slowly until white handle visible. Remove from envelope.

Fig. 1

Or, for a convenient handle protector-

2. Grasp envelope firmly with two hands as shown in Fig. 2. Tear down the middle of envelope to strip.

Fig. 2

Hold the handle end of the strip firmly in the right hand as shown in Fig 3. Hold left edge of paper envelope so that tip is not held between the fingers.

Fig. 3

Snap the left portion off quickly. Strip is ready to use with a convenient handle protector.

Fig. 4

Principal Display Panel Text for Container Label:

NDC 17478-403-03 ONE STERILE STRIP

FUL-GLO® Fluorescein Sodium

Sterile Ophthalmic Strips 0.6 mg

Contents may not be sterile if this package has been damaged or

previously opened. See box for complete information.

Principal Display Panel Text for Carton Label:

NDC 17478-403-03

FUL-GLO®

Fluorescein Sodium

Ophthalmic Strips, USP

0.6 mg

Diagnostic Agent for Professional Use Only

300 Sterile Strips

Akorn Logo